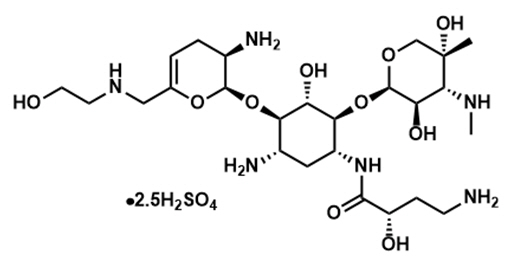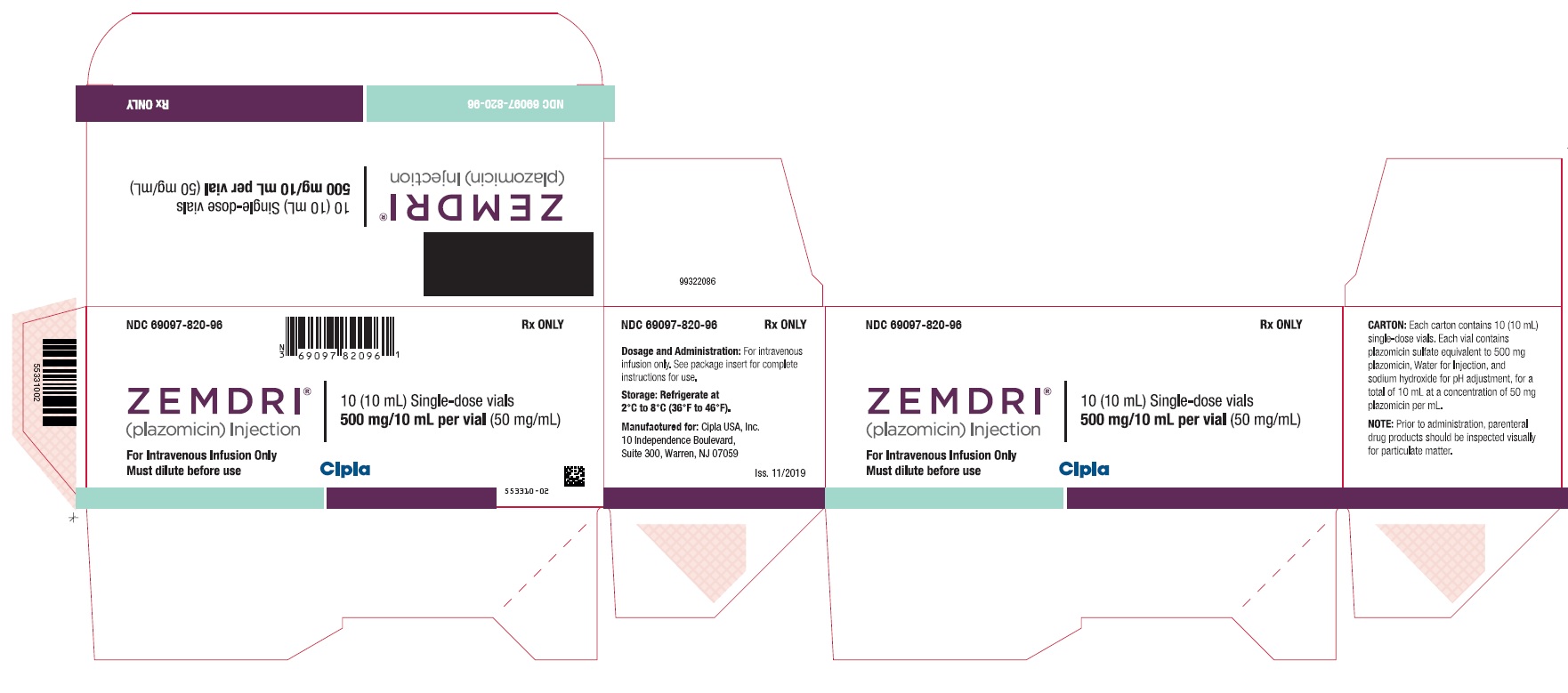 DRUG LABEL: Zemdri (plazomicin)
NDC: 69097-820 | Form: INJECTION
Manufacturer: Cipla USA Inc.
Category: prescription | Type: HUMAN PRESCRIPTION DRUG LABEL
Date: 20241220

ACTIVE INGREDIENTS: plazomicin 500 mg/10 mL
INACTIVE INGREDIENTS: WATER; sodium hydroxide

HIGHLIGHTS OF PRESCRIBING INFORMATION

These highlights do not include all the information needed to use ZEMDRI™® safely and effectively. See full prescribing information for ZEMDRI.
ZEMDRI (plazomicin) injection, for intravenous use
Initial U.S. Approval: 2018

WARNING: NEPHROTOXICITY, OTOTOXICITY, NEUROMUSCULAR BLOCKADE and FETAL HARM

See full prescribing information for complete boxed warning.

- Nephrotoxicity has been reported with ZEMDRI. The risk of nephrotoxicity is greater in patients with impaired renal function, the elderly, and in those receiving concomitant nephrotoxic medications. (5.1)
- Ototoxicity, manifested as hearing loss, tinnitus, and/or vertigo, has been reported with ZEMDRI. Symptoms of aminoglycoside associated ototoxicity may be irreversible and may not become evident until after completion of therapy. (5.2)
- Aminoglycosides have been associated with neuromuscular blockade. During therapy with ZEMDRI, monitor for adverse reactions associated with neuromuscular blockade particularly in high-risk patients. (5.3)
- Aminoglycosides, including ZEMDRI can cause fetal harm when administered to a pregnant woman. (5.6, 8.1)

RECENT MAJOR CHANGES

Warnings and Precautions, Ototoxicity (5.2) | 2/2023

1. INDICATIONS AND USAGE

ZEMDRI is an aminoglycoside antibacterial indicated for the treatment of patients 18 years of age or older with Complicated Urinary Tract Infections (cUTI) including Pyelonephritis. (1.1)

As only limited clinical safety and efficacy data are available, reserve ZEMDRI for use in patients who have limited or no alternative treatment options. (1.1)

To reduce the development of drug-resistant bacteria and maintain effectiveness of ZEMDRI and other antibacterial drugs, ZEMDRI should be used only to treat infections that are proven or strongly suspected to be caused by susceptible microorganisms. (1.2)

2. DOSAGE AND ADMINISTRATION

- Administer ZEMDRI 15 mg/kg every 24 hours by intravenous (IV) infusion over 30 minutes to patients 18 years of age or older with creatinine clearance greater than or equal to 90 mL/min. (2.1)
- Recommended duration of treatment is 4 to 7 days for cUTI, including pyelonephritis. (2.1)
- Assess creatinine clearance in all patients prior to initiating therapy and daily during therapy. (2.2)
- Recommended initial dosage regimen for patients with renal impairment is shown in the table below. (2.3)

Estimated CLcr [CLcr estimated by the Cockcroft-Gault formula. (2.3)] (mL/min) | Recommended Dosage for ZEMDRI [Calculate dosage using Total Body Weight (TBW). For patients with TBW greater than IBW by 25% or more, use adjusted body weight. (2.3)] | Dosing Interval
Greater than or equal to 60 to less than 90 | 15 mg/kg | Every 24 hours
Greater than or equal to 30 to less than 60 | 10 mg/kg | Every 24 hours
Greater than or equal to 15 to less than 30 | 10 mg/kg | Every 48 hours

- See Full Prescribing Information for subsequent dosage adjustment based on changes in renal function or Therapeutic Drug Monitoring (TDM). (2.3, 2.4).
- See Full Prescribing Information for instructions on preparation of the solution, stability in intravenous fluids and drug compatibilities. (2.5, 2.6, 2.7)

3. DOSAGE FORMS AND STRENGTHS

ZEMDRI injection 500 mg/10 mL (50 mg/mL) is a single-dose vial containing plazomicin sulfate equivalent to 500 mg plazomicin free base. (3)

4. CONTRAINDICATIONS

ZEMDRI is contraindicated in patients with known hypersensitivity to any aminoglycoside (4, 5.4)

5. WARNINGS AND PRECAUTIONS

- Hypersensitivity Reactions, including anaphylaxis: Reported for aminoglycosides. If an allergic reaction occurs, discontinue ZEMDRI. (5.4)
- Clostridium difficile-Associated Diarrhea: Reported for nearly all systemic antibacterial drugs. Evaluate if diarrhea occurs. (5.5)

6. ADVERSE REACTIONS

Most common adverse reactions (≥ 1% of patients treated with ZEMDRI) are decreased renal function, diarrhea, hypertension, headache, nausea, vomiting and hypotension. (6.1)

To report SUSPECTED ADVERSE REACTIONS, contact Cipla USA, Inc. at 1-866-604-3268 or FDA at 1-800-FDA-1088 or www.fda.gov/medwatch.

FULL PRESCRIBING INFORMATION

WARNING: NEPHROTOXICITY, OTOTOXICITY, NEUROMUSCULAR BLOCKADE and FETAL HARM

- Nephrotoxicity has been reported with ZEMDRI. The risk of nephrotoxicity is greater in patients with impaired renal function, the elderly, and in those receiving concomitant nephrotoxic medications. Assess creatinine clearance in all patients prior to initiating therapy and daily during therapy [see Dosage and Administration (2.2) and Warnings and Precautions (5.1)]. Therapeutic Drug Monitoring (TDM) is recommended for complicated urinary tract infection (cUTI) patients with CLcr less than 90 mL/min to avoid potentially toxic levels [see Dosage and Administration (2.3, 2.4)].
- Ototoxicity, manifested as hearing loss, tinnitus, and/or vertigo, has been reported with ZEMDRI. Symptoms of aminoglycoside-associated ototoxicity may be irreversible and may not become evident until after completion of therapy. Aminoglycoside-associated ototoxicity has been observed primarily in patients with a family history of hearing loss, patients with renal impairment, and in patients receiving higher doses and/or longer durations of therapy than recommended [see Warnings and Precautions (5.2)].
- Aminoglycosides have been associated with neuromuscular blockade. During therapy with ZEMDRI, monitor for adverse reactions associated with neuromuscular blockade, particularly in high-risk patients, such as patients with underlying neuromuscular disorders (including myasthenia gravis) or in patients concomitantly receiving neuromuscular blocking agents [see Warning and Precautions (5.3)].
- Aminoglycosides, including ZEMDRI, can cause fetal harm when administered to a pregnant woman [see Warnings and Precautions (5.4), Use in Specific Populations (8.1)].

1. INDICATIONS AND USAGE

1.1 Complicated Urinary Tract Infections (cUTI), including Pyelonephritis

ZEMDRI is indicated in patients 18 years of age or older for the treatment of complicated urinary tract infections (cUTI), including pyelonephritis caused by the following susceptible microorganism(s): Escherichia coli, Klebsiella pneumoniae, Proteus mirabilis, and Enterobacter cloacae.

As only limited clinical safety and efficacy data for ZEMDRI are currently available, reserve ZEMDRI for use in cUTI patients who have limited or no alternative treatment options [see Clinical Studies (14.1)].

1.2 Usage

To reduce the development of drug-resistant bacteria and maintain the effectiveness of ZEMDRI and other antibacterial drugs, ZEMDRI should be used only to treat or prevent infections that are proven or strongly suspected to be caused by susceptible bacteria. When culture and susceptibility information are available, they should be considered in selecting or modifying antibacterial therapy. In the absence of such data, local epidemiology and susceptibility patterns may contribute to the empiric selection of therapy.

2. DOSAGE AND ADMINISTRATION

2.1 Recommended Dosage

The recommended dosage regimen of ZEMDRI is 15 mg/kg administered every 24 hours by intravenous (IV) infusion over 30 minutes in patients 18 years of age or older and with creatinine clearance (CLcr) greater than or equal to 90 mL/min (Table 1). The duration of therapy should be guided by the severity of infection and the patient's clinical status for up to 7 days. During treatment, dosage adjustments may be required based on change in renal function [see Dosage and Administration (2.3, 2.4)].

Table 1: Dosage Regimen of ZEMDRI in Adults With CLcr [CLcr estimated by the Cockcroft-Gault formula using total body weight (TBW). For patients with TBW greater than ideal body weight (IBW) by 25% or more, use IBW.] Greater Than or Equal to 90 mL/min
cUTI Infection | Dosage Regimen [Calculate dosage using TBW. For patients with TBW greater than IBW by 25% or more, use adjusted body weight based on the equation: Adjusted body weight = IBW + 0.4 × [TBW – IBW].] | Duration of Treatment
Complicated Urinary Tract Infections, including Pyelonephritis | 15 mg/kg every 24 hours | 4 to 7 days [An appropriate oral therapy may be considered after 4 to 7 days of ZEMDRI therapy to complete a total duration of 7 to 10 days (IV plus oral). The maximum duration of ZEMDRI for cUTI is 7 days.]

2.2 Monitoring of Renal Function

Assess creatinine clearance in all patients prior to initiating therapy and daily during therapy with ZEMDRI [see Dosage and Administration (2.3),Warnings and Precautions (5.1) and Use in Specific Populations (8.6)].

2.3 Dosage in Adult Patients With Renal Impairment

The recommended initial dosage regimen of ZEMDRI in adult patients with CLcr greater than or equal to 15 and less than 90 mL/min, estimated by the Cockcroft-Gault formula, is described in Table 2.

Patients with CLcr greater than or equal to 15 and less than 90 mL/min receiving ZEMDRI may require subsequent dosage adjustments based on change in renal function and/or Therapeutic Drug Monitoring (TDM) as appropriate [see Dosage and Administration (2.4)].

Table 2: Dosage Regimen of ZEMDRI in Adults With CLcr Less Than 90 mL/min
Estimated CLcr [CLcr estimated by the Cockcroft-Gault formula using total body weight (TBW). For patients with TBW greater than ideal body weight (IBW) by 25% or more, use IBW.] (mL/min) | Dosage [Calculate dosage using TBW. For patients with TBW greater than IBW by 25% or more, use adjusted body weight based on the equation: Adjusted body weight = IBW + 0.4 × [TBW – IBW].] | Dosing Interval
Greater than or equal to 60 to less than 90 | 15 mg/kg | Every 24 hours
Greater than or equal to 30 to less than 60 | 10 mg/kg | Every 24 hours
Greater than or equal to 15 to less than 30 | 10 mg/kg | Every 48 hours

There is insufficient information to recommend a dosage regimen in patients with CLcr less than 15 mL/min or on renal replacement therapy, including hemodialysis or continuous renal replacement therapy.

2.4 TDM in cUTI Patients With Renal Impairment

For cUTI patients with CLcr greater than or equal to 15 mL/min and less than 90 mL/min, TDM is recommended to maintain plasma trough concentrations below 3 mcg/mL. Measure plazomicin plasma trough concentration within approximately 30 minutes before administration of the second dose of ZEMDRI. Adjustment of the ZEMDRI dosage regimen based on TDM involves extending ZEMDRI dosing interval by 1.5 fold (i.e., from every 24 hours to every 36 hours or from every 48 hours to every 72 hours) for patients with plasma trough concentrations greater than or equal to 3 mcg/mL [see Warnings and Precautions (5.1) and Clinical Pharmacology (12.2)].

2.5 Preparation of Diluted Solutions of ZEMDRI

ZEMDRI is supplied as a single-dose fliptop 10-mL vial that contains plazomicin sulfate equivalent to 500 mg plazomicin freebase in 10 mL Water for Injection (concentration of 50 mg/mL). The appropriate volume of ZEMDRI solution (50 mg/mL) for the required dose should be diluted in 0.9% Sodium Chloride Injection, USP or Lactated Ringer's Injection, USP to achieve a final volume of 50 mL for intravenous infusion. The stability of ZEMDRI solution in the compatible diluents is described below [see Dosage and Administration (2.7)].

ZEMDRI does not contain preservatives. Aseptic technique must be followed in preparing the infusion solution. Discard unused portion of the ZEMDRI vial.

Parenteral drug products should be inspected visually for particulate matter and discoloration prior to administration, whenever solution and container permit.

2.6 Stability of ZEMDRI Solution in Intravenous Fluids

After dilution, ZEMDRI solution for administration is stable for 24 hours at room temperature, and for up to 7 days when refrigerated at 2°C to 8°C (36°F to 46°F), at concentrations of 2.5 mg/mL to 45 mg/mL in the following solutions:

- 0.9% Sodium Chloride Injection, USP
- Lactated Ringer's Injection, USP

2.7 Drug Compatibility

Compatibility of ZEMDRI for administration with other drugs has not been established. ZEMDRI should not be mixed with other drugs or physically added to solutions containing other drugs. Other medications should not be infused simultaneously with ZEMDRI through the same IV line.

3. DOSAGE FORMS AND STRENGTHS

ZEMDRI injection 500 mg/10 mL (50 mg/mL) is a sterile, clear, colorless to yellow solution supplied in a single-dose vial. Each single-dose vial contains plazomicin sulfate equivalent to 500 mg plazomicin freebase.

4. CONTRAINDICATIONS

ZEMDRI is contraindicated in patients with known hypersensitivity to any aminoglycoside [see Warnings and Precautions (5.5)].

5. WARNINGS AND PRECAUTIONS

5.1 Nephrotoxicity

Nephrotoxicity has been reported with the use of ZEMDRI [see Adverse Reactions (6.1)]. Most serum creatinine increases were ≤ 1 mg/dL above baseline and reversible.

In Trial 1, the incidence of adverse reactions associated with renal function (acute kidney injury, serum creatinine increased, chronic kidney disease, creatinine clearance decreased, renal failure, renal impairment) was 3.6% (11/303) in ZEMDRI-treated patients compared with 1.3% (4/301) in meropenem-treated patients [see Adverse Reactions (6.1)].

Serum creatinine increases of 0.5 mg/dL or greater above baseline occurred in 7% (21/300) of ZEMDRI-treated patients compared with 4% (12/297) of meropenem-treated patients. These increases mainly occurred in patients with CLcr ≤ 90 mL/min and were associated with a plazomicin trough level (Cmin) greater than or equal to 3 mcg/mL [see Adverse Reactions (6.1) and Clinical Pharmacology (12.2)].

Assess CLcr in all patients prior to initiating therapy and daily during therapy with ZEMDRI, particularly in those at increased risk of nephrotoxicity, such as those with renal impairment, the elderly, and those receiving concomitant potentially nephrotoxic medications. In the setting of worsening renal function, the benefit of continuing ZEMDRI should be assessed [see Dosage and Administration (2.2, 2.4), Adverse Reactions (6.1) and Use in Specific Populations (8.5, 8.6)].

Adjust the initial dosage regimen in cUTI patients with CLcr ≥ 15 mL/min and < 60 mL/min [see Dosage and Administration (2.3)]. For subsequent doses, TDM is recommended for patients with CLcr ≥15 mL/min and < 90 mL/min [see Dosage and Administration (2.4)].

5.2 Ototoxicity

Ototoxicity with use of ZEMDRI

Ototoxicity, manifested as hearing loss, tinnitus, and/or vertigo, has been reported with ZEMDRI. Symptoms of aminoglycoside-associated ototoxicity may be irreversible and may not become evident until after completion of therapy.

Regarding the incidence of adverse reactions associated with cochlear or vestibular function, in Trial 1, there was one case of reversible hypoacusis (1/303;0.3%) in ZEMDRI-treated patients and one case of tinnitus (1/301;0.3%) in meropenem-treated patients [see Adverse Reactions (6.1)]. In Trial 2, one case each of irreversible tinnitus and reversible vertigo was reported in ZEMDRI-treated patients, and one case of an abnormal audiogram occurred in a levofloxacin-treated patient [see Adverse Reactions (6.1)].

Aminoglycoside-associated ototoxicity has been observed primarily in patients with a family history of hearing loss (excluding age-related hearing loss), patients with renal impairment, and in patients receiving higher doses and/or for longer periods than recommended. In Trial 1 and Trial 2, patients with a history of hearing loss, with the exception of age-related hearing loss, were excluded. The benefit-risk of ZEMDRI therapy should be considered in these patients.

Risk of Ototoxicity Due to Mitochondrial DNA Variants

Cases of ototoxicity with aminoglycosides have been observed in patients with certain variants in the mitochondrially encoded 12S rRNA gene (MT-RNR1), particularly the m.1555A>G variant. Ototoxicity occurred in some patients even when their aminoglycoside serum levels were within the recommended range. Mitochondrial DNA variants are present in less than 1% of the general US population, and the proportion of the variant carriers who may develop ototoxicity as well as the severity of ototoxicity is unknown. In case of known maternal history of ototoxicity due to aminoglycoside use or a known mitochondrial DNA variant in the patient, consider alternative treatments other than aminoglycosides unless the increased risk of permanent hearing loss is outweighed by the severity of infection and lack of safe and effective alternative therapies.

5.3 Neuromuscular Blockade

Aminoglycosides have been associated with exacerbation of muscle weakness in patients with underlying neuromuscular disorders, or delay in recovery of neuromuscular function in patients receiving concomitant neuromuscular blocking agents.

During therapy with ZEMDRI, monitor for adverse reactions associated with neuromuscular blockade, particularly in high-risk patients, such as patients with underlying neuromuscular disorders (including myasthenia gravis) or those patients concomitantly receiving neuromuscular blocking agents.

5.4 Fetal Harm

Aminoglycosides, including ZEMDRI, can cause fetal harm when administered to a pregnant woman. Aminoglycosides cross the placenta, and streptomycin has been associated with several reports of total, irreversible, bilateral congenital deafness in pediatric patients exposed in utero. Patients who use ZEMDRI during pregnancy, or become pregnant while taking ZEMDRI should be apprised of the potential hazard to the fetus [see Use in Specific Populations (8.1)].

5.5 Hypersensitivity Reactions

Serious and occasionally fatal hypersensitivity (anaphylactic) reactions have been reported in patients receiving aminoglycoside antibacterial drugs. Before therapy with ZEMDRI is instituted, careful inquiry about previous hypersensitivity reactions to other aminoglycosides should be made. A history of hypersensitivity to other aminoglycosides is a contraindication to the use of ZEMDRI, because cross-sensitivity among aminoglycoside antibacterial drugs has been established. Discontinue ZEMDRI if an allergic reaction occurs.

5.6 Clostridium difficile-Associated Diarrhea

Clostridium difficile-associated diarrhea (CDAD) has been reported for nearly all systemic antibacterial drugs and may range in severity from mild diarrhea to fatal colitis. Treatment with antibacterial drugs alters the normal flora of the colon and may permit overgrowth of C. difficile.

C. difficile produces toxins A and B that contribute to the development of CDAD. Hypertoxin-producing strains of C. difficile cause increased morbidity and mortality, as these infections can be refractory to antimicrobial therapy and may require colectomy. CDAD must be considered in all patients who present with diarrhea following antibacterial use. Careful medical history is necessary because CDAD has been reported to occur more than 2 months after the administration of antibacterial drugs.

If CDAD is suspected or confirmed, antibacterial drugs not directed against C. difficile may need to be discontinued. Manage fluid and electrolyte levels as appropriate, supplement protein intake, monitor antibacterial treatment of C. difficile, and institute surgical evaluation as clinically indicated.

5.7 Development of Drug-Resistant Bacteria

Prescribing ZEMDRI in the absence of a proven or strongly suspected bacterial infection is unlikely to provide benefit to the patient and increases the risk of the development of drug-resistant bacteria.

6. ADVERSE REACTIONS

The following important adverse reactions are discussed in greater detail in the Warnings and Precautions section:

- Nephrotoxicity [see Warnings and Precautions (5.1)]
- Ototoxicity [see Warnings and Precautions (5.2)]
- Neuromuscular Blockade [see Warnings and Precautions (5.3)]
- Fetal Harm [see Warnings and Precautions (5.4)]
- Hypersensitivity Reactions [see Warnings and Precautions (5.5)]
- Clostridium difficile-Associated Diarrhea [see Warnings and Precautions (5.6)]

6.1 Clinical Trial Experience

Because clinical trials are conducted under widely varying conditions, adverse reaction rates observed in the clinical trials of a drug cannot be compared directly to rates in the clinical trials of another drug and may not reflect the rates observed in practice.

ZEMDRI was evaluated in two comparator-controlled clinical trials (Trial 1, NCT02486627 and Trial 2, NCT01096849) in patients with cUTI, including pyelonephritis. In both trials, patients with CLcr greater than 60 mL/min received ZEMDRI 15 mg/kg IV once daily as a 30-minute infusion [see Clinical Studies (14.1)].

Trial 1 included 303 patients treated with ZEMDRI and 301 patients treated with meropenem. Patients were to receive 4 to 7 days of ZEMDRI (mean duration of 5.1 days). In some patients, parenteral therapy was followed by a switch to an oral antibacterial drug.

The median age of patients treated with ZEMDRI in Trial 1 was 62 years (range 18 to 90 years) and 45.2% of patients were 65 years of age or older. Patients treated with ZEMDRI were predominantly female (56.1%) and White (99.3%). A majority of patients (68.0%) had mild or moderate renal impairment (CLcr >30 to 90 mL/min) at baseline. Patients with CLcr of 30 mL/min or less were excluded.

Adverse Reactions Leading to Treatment Discontinuations in Trial 1

In Trial 1, treatment discontinuation from IV study drug due to an adverse reaction occurred in 2.0% of patients receiving ZEMDRI (6/303) and meropenem (6/301), respectively.

Common Adverse Reactions in Trial 1

Table 3 lists adverse reactions occurring in 1% or more of patients receiving ZEMDRI in Trial 1.

Table 3: Incidence (%) of Adverse Reactions Occurring in 1% or More of cUTI Adult Patients Treated With ZEMDRI in Trial 1
Adverse Reactions | ZEMDRI (N=303) n (%) | Meropenem [1 g IV every 8 hours.] (N=301) n (%)
Decreased Renal Function [Combined term that corresponds to adverse reactions associated with renal function described in Nephrotoxicity section below.] | 11 (3.6) | 4 (1.3)
Diarrhea | 7 (2.3) | 5 (1.7)
Hypertension | 7 (2.3) | 7 (2.3)
Headache | 4 (1.3) | 9 (3.0)
Nausea | 4 (1.3) | 4 (1.3)
Vomiting | 4 (1.3) | 3 (1.0)
Hypotension | 3 (1.0) | 2 (0.7)

The adverse reactions profile for the cUTI patients in Trial 2 were similar to those observed in Trial 1.

Nephrotoxicity Reported in Trial 1

In Trial 1, serum creatinine increases of 0.5 mg/dL or greater above baseline occurred in 7.0% (21/300) of ZEMDRI-treated patients compared with 4.0% (12/297) of meropenem-treated patients. Of these, the incidence during IV therapy was 3.7% (11/300) vs 3.0% (9/297) in ZEMDRI- and meropenem-treated patients, respectively. By the last follow-up visit (between 8 to 43 days after completion of IV therapy), the majority of ZEMDRI-treated patients (9/11) and all meropenem treated patients (9/9) with serum creatinine increases while on therapy had fully recovered renal function. Serum creatinine increases of 0.5 mg/dL or greater above baseline were observed following completion of IV therapy. These increases were generally ≤ 1.0 mg/dL above baseline and recovered by the next measurement.

In cUTI patients with CLcr of greater than 30 and less than or equal to 90 mL/min, 9.7% (20/207) ZEMDRI-treated and 4.1% (9/217) meropenem-treated patients had serum creatinine increases of 0.5 mg/dL or greater above baseline. In cUTI patients with CLcr greater than 90 mL/min, 1.1% (1/93) ZEMDRI-treated and 3.8% (3/80) of meropenem-treated patients had serum creatinine increases of 0.5 mg/dL or greater above baseline [see Use in Specific Populations (8.6)].

Ototoxicity

Pure tone audiometry was evaluated in Phase 1 trials and in Trial 2. Treatment associated ototoxicity could not be definitively excluded according to the American Speech-Language-Hearing Association criteria^1 in 2.2% (4/182) of ZEMDRI-exposed and 2.0% (1/49) of comparator- or placebo-exposed adults.

Other Adverse Reactions Reported with ZEMDRI

The following selected adverse reactions were reported in more than one ZEMDRI-treated patient in Trials 1 and 2 and are not described elsewhere in the labeling:

Gastrointestinal disorders: constipation, gastritis

Laboratory Investigations: alanine aminotransferase increased

Metabolism and nutrition disorders: hypokalemia

Nervous system disorders: dizziness

Renal and urinary disorders: hematuria

Respiratory, thoracic and mediastinal disorders: dyspnea

8. USE IN SPECIFIC POPULATIONS

8.1 Pregnancy

Risk Summary

Aminoglycosides, including ZEMDRI, can cause fetal harm when administered to a pregnant woman. There are no available data on the use of ZEMDRI in pregnant women to inform a drug associated risk of adverse developmental outcomes. Published literature reports of streptomycin, an aminoglycoside, state that it can cause total, irreversible, bilateral congenital deafness in children whose mothers received streptomycin during pregnancy. No drug-related visceral or skeletal malformations were observed in pregnant rats and rabbits administered subcutaneous plazomicin during organogenesis at maternal exposures approximately 0.8-fold (rats) and 2.5-fold (rabbits) of the human AUC at the clinical dose of 15 mg/kg/day. Auditory function of offspring was not measured in animal studies (see Data). Advise pregnant women of the potential risk to a fetus.

The background risk of major birth defects and miscarriage for the indicated population is unknown. In the U.S. general population, the estimated background risk of major birth defects and miscarriage in clinically recognized pregnancies is 2% to 4% and 15% to 20%, respectively.

Data

Animal Data

In an embryo-fetal development study in rats, plazomicin doses of 0, 8, 25, or 50 mg/kg/day administered subcutaneously during organogenesis did not cause drug-related visceral or skeletal malformations, or reduce survival of fetuses. The mid and high doses caused maternal toxicity (reductions in food consumption and body weight gain; increased kidney weight). The high dose resulted in maternal exposure (AUC) approximately 0.8-fold the human AUC at the clinical dose of 15 mg/kg once daily.

In an embryo-fetal development study in rabbits, plazomicin administered subcutaneously at doses of 0, 10, 30, or 50 mg/kg/day did not cause visceral or skeletal malformations or reduced fetal survival. At the high dose, significant maternal toxicity was observed (including renal injury and lethality) and exposure was approximately 2.5-fold the human AUC at the recommended clinical dose.

In a pre- and postnatal development study in rats, maternal animals received subcutaneous plazomicin at 0, 3, 8, or 30 mg/kg/day from the start of organogenesis through lactation. There were no adverse effects on maternal function or pre- and postnatal survival, development, behavior, or reproductive function of the offspring at up to 30 mg/kg/day (0.32-fold human AUC at the clinical daily dose of 15 mg/kg).

8.2 Lactation

Risk Summary

There are no data on the presence of ZEMDRI in human milk, the effects on the breastfed infant, or the effects on milk production. Plazomicin was detected in rat milk (see Data). The developmental and health benefits of breastfeeding should be considered along with the mother's clinical need for ZEMDRI and any potential adverse effects on the breastfed infant from ZEMDRI or from the underlying maternal condition.

Data

In a pre- and postnatal development study in rats, low concentrations of plazomicin in maternal milk were detected, with mean concentrations representing 2% to 4% of maternal plasma concentrations. In nursing pups, the systemic exposure (AUC) to plazomicin through lactational exposure was approximately 0.04% of maternal systemic exposure.

8.4. Pediatric Use

The safety and effectiveness of ZEMDRI in patients less than 18 years of age have not been established.

8.5 Geriatric Use

Of the 425 patients treated with ZEMDRI in Trials 1 and 2, 40% (170/425) were 65 years of age and older, including 17.2% (73/425) patients 75 years of age and older. In Trial 1, for ZEMDRI- treated patients ≥ 65 years old, the incidence rate of adverse reactions was 27% (37/137) versus 18.9% (27/143) in the meropenem-treated patients ≥ 65 years old. For ZEMDRI- treated patients < 65 years old, the incidence rate of adverse reactions was 13.3% (22/166) versus 24.1% (38/158) in the meropenem-treated patients < 65 years old.

The rate of adverse reactions associated with renal function for the ZEMDRI-treated patients ≥ 65 years old was 6.6% (9/137) versus 2.8% (4/143) in the meropenem-treated patients. For ZEMDRI- treated patients < 65 years old, the incidence rate of adverse reactions associated with renal function was 1.2% (2/166), versus 0% (0/158) in the meropenem-treated patients [see Clinical Studies (14.1) and Adverse Reactions (6.1)].

ZEMDRI is substantially excreted by the kidneys, and the risk of adverse reactions to ZEMDRI may be greater in patients with renal impairment. Because elderly patients are more likely to have decreased renal function, care should be taken in dose selection, and renal function should be monitored. Dosage adjustment in elderly patients should take into account renal function and plazomicin concentrations as appropriate [see Dosage and Administration (2.2, 2.3, 2.4) and Clinical Pharmacology (12.3)].

8.6 Renal Impairment

Plazomicin total body clearance was significantly decreased in patients with CLcr greater than or equal to 15 to less than 60 mL/min compared to patients with CLcr greater than or equal to 60 mL/min [see Clinical Pharmacology (12.3)]. Monitor CLcr daily and adjust ZEMDRI dosage accordingly [see Dosage and Administration (2.2)]. There is insufficient information to recommend a dosage regimen in patients with CLcr less than 15 mL/min or on renal replacement therapy, including hemodialysis or continuous renal replacement therapy.

For patients with CLcr greater than or equal to 15 mL/min and less than 90 mL/min, TDM is recommended. Monitor plazomicin trough concentrations and adjust ZEMDRI dosage accordingly [see Dosage and Administration (2.3, 2.4)].

10. OVERDOSAGE

In the event of overdosage, ZEMDRI should be discontinued and supportive care is advised. Maintenance of glomerular filtration and careful monitoring of renal function is recommended. Hemodialysis may aid in the removal of ZEMDRI from the blood, especially if renal function is, or becomes, compromised. No clinical information is available on the use of hemodialysis to treat ZEMDRI overdosage.

11. DESCRIPTION

ZEMDRI contains plazomicin sulfate, a semi-synthetic aminoglycoside antibacterial derived from sisomicin. The chemical name of plazomicin sulfate is (2"R,3"R,4"R,5"R)-2"-[(1S,2S,3R,4S,6R)-4-amino-6-[(2'"S)-4'"-amino-2'"-hydroxybutanamido)amino]-3-[(2'S,3'R)-3'-amino-6'-((2-hydroxyethylamino)methyl)-3',4'-dihydro-2H-pyran-2'-yloxy]-2-hydroxycyclohexyloxy]-5''-methyl-4''-(methylamino)tetrahydro-2H-pyran-3'',5''-diol sulfate. Plazomicin sulfate contains a theoretical 2.5 molar equivalents of sulfate relative to the freebase, based on complete protonation. The molecular weight of plazomicin sulfate is calculated based on 1:2.5 stoichiometry. The corresponding empirical formula is C25H48N6O10∙2.5 H2SO4 (plazomicin sulfate) and the molecular weight of the plazomicin sulfate salt is 837.89 g/mol and the molecular weight of the freebase is 592.69 g/mol.

Figure 1: Chemical Structure of Plazomicin Sulfate

ZEMDRI injection 500 mg/10 mL is a sterile, clear, colorless-to-yellow liquid for intravenous administration supplied in 10-mL single-dose Type 1 glass vials. Each vial contains plazomicin sulfate equivalent to 500 mg plazomicin freebase at a concentration of 50 mg/mL adjusted to pH 6.5. Each vial also contains Water for Injection and sodium hydroxide for pH adjustment. This sterile, nonpyrogenic solution is formulated without preservatives.

12. CLINICAL PHARMACOLOGY

12.1 Mechanism of Action

ZEMDRI is an antibacterial drug [see Microbiology (12.4)].

12.2 Pharmacodynamics

The ratio of area under the plasma concentration-time curve to the minimum inhibitory concentration (AUC:MIC) for plazomicin has been shown to best correlate with efficacy in animal and in vitro models of infection against Enterobacteriaceae.

Exposure- Response Relationship for Nephrotoxicity in cUTI Patients

Based on exposure-response analysis for nephrotoxicity, defined as serum creatinine increases greater than or equal to 0.5 mg/dL from baseline, using the data from two cUTI clinical trials (Trial 1 and Trial 2), development of nephrotoxicity was associated with estimated plazomicin exposure (i.e., the plasma trough concentration [Cmin]) in patients with CLcr greater than 30 mL/min and less than or equal to 90 mL/min (N=243). The incidence of nephrotoxicity was higher in patients with plazomicin Cmin greater than or equal to 3 mcg/mL (36%, 10/28) compared to patients with plazomicin Cmin less than 3 mcg/mL (5%, 11/215).

Cardiac Electrophysiology

The effect of ZEMDRI on the QTc interval was evaluated in a Phase 1 randomized, placebo and positive controlled, double-blind, single-dose, crossover thorough QTc study in 56 healthy adult subjects. At a single dose of 20 mg/kg (1.3 times the maximum recommended dose), ZEMDRI did not prolong the QTc interval to any clinically relevant extent.

12.3 Pharmacokinetics

The pharmacokinetic (PK) parameters of plazomicin are similar for single- and multiple-dose administration of ZEMDRI in healthy subjects. No appreciable accumulation of plazomicin was observed following multiple IV infusions of 15 mg/kg administered every 24 hours in subjects with normal renal function. The AUC, maximum plasma concentration (Cmax), and Cmin increased in proportion to the dose over the dose range of 4 to 15 mg/kg. The plazomicin AUC, Cmax, and Cmin are summarized in Table 4.

Table 4: Pharmacokinetic Parameters (Geometric Mean [±SD]) of Plazomicin Following Administration of ZEMDRI 15 mg/kg by 30-Minute IV Infusion in Healthy Subjects and cUTI Patients with CLcr Greater than or Equal to 90 mL/min
 | Healthy Subjects [PK parameters following a single dose of 15 mg/kg; Based on non-compartmental analysis of PK data; AUC0-inf is reported; Cmin is concentration at 24 hours.] Geometric mean (±SD) N=54 | cUTI Patients [Day 1 PK parameters following administration of 15 mg/kg; Derived based on population PK model; AUC0-24h is reported.] Geometric mean (±SD) N=87
AUC (mcg∙h/mL) | 257 (±67.0) | 226 (±113)
Cmax (mcg/mL) | 73.7 (±19.7) | 51.0 (±26.7)
Cmin (mcg/mL) | 0.3 (±0.2) | 0.5 (±1.2)

Distribution

The mean (±SD) volume of distribution of plazomicin in healthy adults and cUTI patients is 17.9 (±4.8) and 30.8 (±12.1) L, respectively. The average binding of plazomicin to human plasma proteins is approximately 20%. The degree of protein binding was concentration-independent across the range tested in vitro (5 to 100 mcg/mL).

Elimination

The mean (±SD) total body clearance of plazomicin in healthy adults and cUTI patients is 4.5 (±0.9) and 5.1 (±2.01) L/h, respectively. The mean (±SD) half-life of plazomicin was 3.5 h (±0.5) in healthy adults with normal renal function (n=54).

Metabolism

Plazomicin does not appear to be metabolized to any appreciable extent.

Excretion

Plazomicin is primarily excreted by the kidneys. Following a single 15 mg/kg IV dose of radiolabeled plazomicin in healthy subjects, 56% of the total administered radioactivity was recovered in urine within 4 hours, 89.1% was recovered within 168 hours, with less than 0.2% in feces. In total, 97.5% of the dose was recovered in the urine as unchanged plazomicin. The mean renal clearance (±SD) of plazomicin (4.6 [±1.2] L/h) was similar to total body clearance, suggesting that plazomicin is eliminated by the kidneys.

Specific Populations

No clinically significant differences in the pharmacokinetics of plazomicin were observed based on age (18 to 90 years of age), sex, or race/ethnicity. The pharmacokinetics of plazomicin in patients with hepatic impairment is unknown.

Patients with Renal Impairment

Following a single 7.5 mg/kg IV dose (0.5 times the recommended dose) of ZEMDRI as a 30-minute infusion, the geometric mean AUC0-inf of plazomicin in subjects with mild (CLcr 60 to <90 mL/min, n=6), moderate (CLcr 30 to <60 mL/min, n=6), and severe (CLcr 15 to <30 mL/min, n=6) renal impairment was 1.01-fold, 1.98-fold, and 4.42-fold higher, respectively, compared to subjects with normal renal function (CLcr ≥90 mL/min, n=6) [see Dosage and Administration (2.2) and Use in Specific Populations (8.6)].

Based on the population PK model, the recommended dosage of ZEMDRI was associated with a mean (±SD) Cmin of 1.0 (±1.3) and 1.7 (±1.4) mcg/mL in cUTI patients with mild (CLcr 60 to <90 mL/min, n=104) and moderate (CLcr 30 to <60 mL/min, n=89) renal impairment, respectively. The mean (±SD) area under the curve from time zero to 24 hours (AUC0-24h) was 261 (±102) and 224 (±147) mcg∙h/mL in cUTI patients with mild (CLcr 60 to <90 mL/min, n=104) and moderate (CLcr 30 to <60 mL/min, n=89) renal impairment, respectively. There were insufficient data to calculate Cmin and AUC0-24h for patients with severe renal impairment (CLcr 15 to <30 mL/min).

Geriatric Patients

No clinically relevant trend in plazomicin exposure (Cmax and AUC0-24h) was observed with regard to age alone. Higher Cmin in elderly subjects (65 to 90 years of age) as compared to non-elderly adult subjects (18 to 64 years of age) was mainly attributable to age-related changes in renal function [see Dosage and Administration (2.2) and Use in Specific Populations (8.5)].

Drug Interaction Studies

Clinical Studies

Based on the results of a clinical drug-drug interaction (DDI) study that evaluated the effect of a single dose of plazomicin (15 mg/kg) on the single dose plasma PK of metformin, plazomicin did not affect the PK of metformin, which is a substrate of OCT and MATE transporters.

In Vitro Studies

Drug-Metabolizing Enzymes

Plazomicin does not inhibit the following cytochrome P450 isoforms: CYP1A2, CYP2B6, CYP2C8, CYP2C9, CYP2C19, CYP2D6, and CYP3A4/5. Plazomicin does not induce CYP1A2, CYP2B6, and CYP3A4.

Membrane Transporters

Plazomicin is not a substrate of P-gp or BCRP transporters. Plazomicin does not inhibit the following hepatic and renal transporters in vitro at clinically relevant concentrations: P-gp, BCRP, BSEP, MRP2, OATP1B1, OATP1B3, OAT1, OAT3, OCT1, and OCT2. Plazomicin selectively inhibited the MATE1 and MATE2-K renal transporter in vitro with an IC50 value of 1300 and 338 mcg/mL, respectively.

12.4 Microbiology

Mechanism of Action

Plazomicin is an aminoglycoside that acts by binding to bacterial 30S ribosomal subunit, thereby inhibiting protein synthesis. Plazomicin has concentration-dependent bactericidal activity as measured by time kill studies. In vitro studies demonstrated a plazomicin post-antibiotic effect ranging from 0.2 to 2.6 hours at 2× MIC against Enterobacteriaceae.

Resistance

Resistance to aminoglycosides includes production of aminoglycoside modifying enzymes (AMEs), alteration of the ribosomal target through production of 16S rRNA methyltransferases, up-regulation of efflux pumps and reduced permeability into bacterial cell due to loss of outer membrane porins.

Plazomicin is not inhibited by most AMEs known to affect gentamicin, amikacin and tobramycin, including acetyltransferases (AACs), phosphotransferases (APHs) and nucleotidyltransferases (ANTs). Plazomicin, like other aminoglycosides, is inactive against bacterial isolates that produce 16S rRNA methyltransferases. Plazomicin may have reduced activity against Enterobacteriaceae that overexpress certain efflux pumps (e.g., acrAB-tolC) or lower expression of porins (e.g., ompF or ompK36).

Plazomicin has no in vitro activity against streptococci (including Streptococcus pneumoniae), enterococci (including Enterococcus faecalis, E. faecium), anaerobes, Stenotrophomonas maltophilia and Acinetobacter spp and variable activity against Pseudomonas aeruginosa.

Activity of plazomicin was demonstrated in vitro against Enterobacteriaceae in the presence of certain beta-lactamases, including extended-spectrum beta-lactamases (TEM, SHV, CTX-M, AmpC), serine carbapenemases (KPC-2, KPC-3), and oxacillinase (OXA-48). Bacteria producing metallo-beta-lactamases often co-express 16S rRNA methyltransferase, conferring resistance to plazomicin.

Interaction With Other Antimicrobials

In vitro studies have demonstrated that against Enterobacteriaceae isolates, no antagonism was observed for plazomicin in combination with clindamycin, colistin, daptomycin, fosfomycin, levofloxacin, linezolid, rifampin, tigecycline and vancomycin; few isolates showed synergy with ceftazidime, meropenem and piperacillin-tazobactam. The clinical significance of these findings is unknown.

Animal Infection Models

Plazomicin demonstrated activity in animal models of infection (e.g., thigh infection, lung infection, and septicemia) caused by either amikacin-non-susceptible, gentamicin-non-susceptible, or beta-lactamase producing Enterobacteriaceae.

Antimicrobial Activity

ZEMDRI has been shown to be active against most isolates of the following bacteria, both in vitro and in clinical infections [see Indications and Usage (1)]

Aerobic Bacteria

Gram-negative Bacteria

- Escherichia coli
- Klebsiella pneumoniae
- Proteus mirabilis
- Enterobacter cloacae

The following in vitro data are available, but their clinical significance is unknown. At least 90 percent of the following bacteria exhibit in vitro minimum inhibitory concentration (MIC) less than or equal to the susceptible breakpoint for plazomicin against isolates of similar genus or organism group. However, the efficacy of ZEMDRI in treating clinical infections caused by these bacteria has not been established in adequate and well-controlled clinical trials.

Aerobic Bacteria

Gram-negative Bacteria

- Citrobacter freundii
- Citrobacter koseri
- Enterobacter aerogenes
- Klebsiella oxytoca
- Morganella morganii
- Proteus vulgaris
- Providencia stuartii
- Serratia marcescens

Susceptibility Test Methods

For specific information regarding susceptibility test interpretive criteria, and associated test methods and quality control standards recognized by FDA for this drug, please see https://www.fda.gov/STIC

13. NONCLINICAL TOXICOLOGY

13.1 Carcinogenesis, Mutagenesis, and Impairment of Fertility

Carcinogenesis

Long term carcinogenicity studies in animals have not been conducted with plazomicin.

Mutagenesis

Plazomicin was negative for mutagenicity in an Ames test and did not induce chromosome aberrations in cultured human peripheral blood lymphocytes. In vivo, a mouse bone marrow micronucleus assay showed no evidence of clastogenic potential.

Impairment of Fertility

In a fertility and early embryonic development study, male and female rats received subcutaneous plazomicin at 0, 8, 25, or 50 mg/kg/day from prior to pairing through the mating and postmating period. Parental toxicity (reduced food consumption and body weight gain, and gross kidney changes) was observed at the mid and high doses. Plazomicin had no adverse effects on fertility in male rats at up to 50 mg/kg/day, resulting in an exposure (AUC) approximately 0.8-fold the human AUC at the clinical dose of 15 mg/kg once daily. In female rats, there were no effects on estrous cyclicity or reproductive performance including mating indices, fertility and fecundity indices, and copulatory intervals. At 25 and 50 mg/kg/day, female rats had fewer corpora lutea, leading to fewer uterine implantation sites and viable embryos per dam. The no observed effect level (NOEL) for fertility and reproductive performance in female rats was 8 mg/kg/day (0.1-fold human AUC).

14. CLINICAL STUDIES

14.1 Complicated Urinary Tract Infections, Including Pyelonephritis

A total of 609 adults hospitalized with cUTI (including pyelonephritis) were randomized in a multinational, double-blind, noninferiority trial comparing ZEMDRI (15 mg/kg IV once daily as a 30-minute infusion) to meropenem (1 g intravenously every 8 hours as a 30-minute infusion) (Trial 1, NCT02486627). Switch to an oral antibacterial drug, such as levofloxacin, was allowed after a minimum of 4 and maximum of 7 days of IV therapy for a total of 7 to 10 days of treatment.

Efficacy was assessed in the microbiological modified intent-to-treat (mMITT) population, which included all patients who received study medication and had at least 1 baseline uropathogen. The mMITT population excluded patients with organisms resistant to study drugs. Patient demographic and baseline characteristics were balanced between treatment groups in the mMITT population. The mMITT population consisted of 388 patients with cUTI, including 162 (41.8%) with pyelonephritis. The median age was 64 years, 52.8% were female and 99.5% were White. The majority of the patients (99%) were from Eastern Europe; 3 patients were from the United States. Concomitant bacteremia was identified in 25 (13.1%) and 23 (11.7%) patients at baseline in the ZEMDRI and meropenem groups, respectively. The median treatment duration of IV study drug was 6 days in both groups.

ZEMDRI demonstrated efficacy for composite cure at Day 5 and the Test of Cure (TOC) visit (Table 5). Composite cure at Day 5 was defined as resolution or improvement of clinical cUTI symptoms and a microbiological outcome of eradication (all baseline uropathogens reduced to <10^4 colony-forming units [CFU]/mL). Composite cure at the TOC visit (Day 17 ± 2 from the first dose of study drug) was defined as resolution of clinical cUTI symptoms and a microbiological outcome of eradication.

Table 5: Composite Cure Rates in cUTI Patients in Trial 1 (mMITT Population)
Analysis Visit | ZEMDRI n/N (%) | Meropenem n/N (%) | Treatment Difference [Treatment difference is ZEMDRI – meropenem.] (95% CI)
Day 5 | 168/191 (88.0) | 180/197 (91.4) | -3.4 (-10.0, 3.1)
Clinical cure or improvement | 171/191 (89.5) | 182/197 (92.4)
Microbiological eradication | 188/191 (98.4) | 193/197 (98.0)
TOC | 156/191 (81.7) | 138/197 (70.1) | 11.6 (2.7, 20.3)
Clinical Cure | 170/191 (89.0) | 178/197 (90.4)
Microbiological eradication | 171/191 (89.5) | 147/197 (74.6)
Abbreviations: CI=confidence interval; TOC=test-of-cure; CI=95% confidence interval based on Newcombe method with continuity correction.

Microbiological eradication rates at the TOC visit by baseline uropathogen in the mMITT population are presented in Table 6. Composite Cure at the TOC visit in individuals with concomitant bacteremia at baseline was achieved in 72.0% (18/25) of patients in the ZEMDRI group and 56.5% (13/23) of patients in the meropenem group.

Table 6: Microbiological Eradication Rate at TOC by Baseline Pathogen in cUTI Patients in Trial 1 (mMITT Population)
Pathogen | ZEMDRI n/N (%) | Meropenem n/N (%)
All Enterobacteriaceae | 177/198 (89.4) | 157/208 (75.5)
Escherichia coli | 120/128 (93.8) | 106/142 (74.6)
Klebsiella pneumoniae | 27/33 (81.8) | 32/43 (74.4)
Proteus mirabilis | 9/11 (81.8) | 4/7 (57.1)
Enterobacter cloacae | 13/16 (81.3) | 3/3 (100.0)

There were 52 baseline Enterobacteriaceae isolates in 51/189 (27%) patients in the ZEMDRI group that were non-susceptible (defined as intermediate or resistant) to gentamicin, or tobramycin or both. All of these isolates were susceptible to plazomicin and all but one was susceptible to amikacin (one isolate was intermediate to amikacin). The microbiological eradication rate at the TOC visit in this subset was 78.9% (41/52) in the ZEMDRI group. Note that certain resistance mechanisms can confer resistance to all aminoglycosides, including plazomicin [see Microbiology (12.4)].

15. REFERENCES

1. American Speech-Language-Hearing Association. (1994). Audiologic management of individuals receiving cochleotoxic drug therapy [Guidelines]. Available from www.asha.org/policy.

16. HOW SUPPLIED/STORAGE AND HANDLING

16.1 How Supplied

ZEMDRI injection 500 mg/10 mL (50 mg/mL) is supplied in single-dose, 10-mL vials fitted with flip-off seals with royal blue polypropylene buttons as a clear, colorless to yellow, sterile solution. Each vial contains plazomicin sulfate equivalent to 500 mg plazomicin freebase at a concentration of 50 mg/mL plazomicin in Water for Injection. Each vial contains sodium hydroxide for pH adjustment to 6.5. The solution may become yellow in color; this does not indicate a decrease in potency.

NDC number | Package/Volume | Units per carton | Plazomicin content
69097-820-96 | Single use, fliptop vial, 10-mL | 10 | 500 mg in 10 mL (50 mg/mL)

16.2 Storage and Handling

Store ZEMDRI injection 500 mg/10 mL (50 mg/mL) refrigerated at 2°C to 8°C (36°F to 46°F).

17. PATIENT COUNSELING INFORMATION

Nephrotoxicity

Advise patients, their families, or caregivers that nephrotoxicity has been reported with ZEMDRI therapy. Counsel patients to follow their physician's directions regarding renal function laboratory tests, maintenance of adequate hydration, and avoidance of potentially nephrotoxic agents while receiving ZEMDRI therapy [see Warnings and Precautions (5.1)].

Ototoxicity

Advise patients, their families, or caregivers that hearing loss, vertigo, and tinnitus have been reported with ZEMDRI therapy. Counsel patients to inform their physician if they experience changes in hearing or balance, or if they experience new onset or changes in preexisting buzzing or roaring in their ear(s), even if it occurs after the completion of ZEMDRI therapy [see Warnings and Precautions (5.2)].

Aggravation of Neuromuscular Disorders

Advise patients, their families, or caregivers that aggravation of muscle weakness has been reported for other aminoglycosides, particularly in patients with underlying neuromuscular disease or receiving neuromuscular blocking agents. Counsel patients to inform their physician if they have an underlying neuromuscular disorder such as myasthenia gravis or are receiving neuromuscular blocking agents [see Warnings and Precautions (5.3)].

Fetal Harm

Aminoglycosides, including ZEMDRI, can cause fetal harm when administered to a pregnant woman. Counsel women of childbearing potential about the potential risk of fetal harm if ZEMDRI is used during pregnancy. Advise pregnant women that aminoglycosides can cause irreversible congenital deafness when administered to a pregnant woman [see Use in Specific Populations (8.1)]. Tell women of childbearing potential to notify their prescribing physician/ healthcare provider if they become pregnant during ZEMDRI treatment [see Warnings and Precautions (5.4)].

Hypersensitivity Reactions

Advise patients, their families, or caregivers that allergic reactions, including serious allergic reactions, could occur and that serious reactions require immediate treatment. Ask them about any previous hypersensitivity reactions to ZEMDRI or other aminoglycosides [see Warnings and Precautions (5.5)].

Potentially Serious Diarrhea

Advise patients, their families, or caregivers that diarrhea is a common problem caused by antibacterial drugs, including ZEMDRI. Sometimes, frequent watery or bloody diarrhea may occur and may be a sign of a more serious intestinal infection. If severe watery or bloody diarrhea develops, tell patient to contact his or her healthcare provider [see Warnings and Precautions (5.6)].

Antibacterial Resistance

Counsel patients, their families, or caregivers that antibacterial drugs, including ZEMDRI, should only be used to treat bacterial infections. They do not treat viral infections (e.g., the common cold). When ZEMDRI is prescribed to treat a bacterial infection, patients should be told that although it is common to feel better early in the course of therapy, the medication should be taken exactly as directed. Skipping doses or not completing the full course of therapy may (1) decrease the effectiveness of the immediate treatment and (2) increase the likelihood that bacteria will develop resistance and will not be treatable by ZEMDRI or other antibacterial drugs in the future [see Warnings and Precautions (5.7)].

Manufactured for:
Cipla USA, Inc.
Warren, NJ 07059

PRINCIPAL DISPLAY PANEL - 10 mL Vial Carton

NDC 69097-820-96
Rx ONLY

ZEMDRI™
(plazomicin) Injection

10 (10 mL) Single-dose vials
500 mg/10 mL per vial (50 mg/mL)

For Intravenous Infusion Only
Must dilute before use